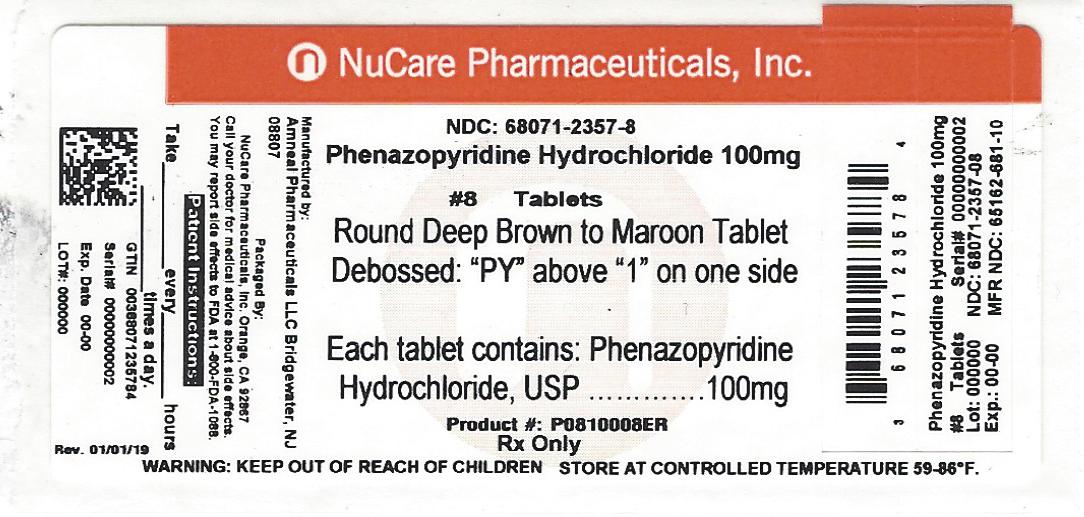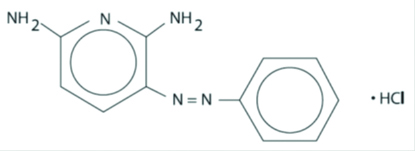 DRUG LABEL: Phenazopyridine Hydrochloride
NDC: 68071-2357 | Form: TABLET
Manufacturer: NuCare Pharmaceuticals,Inc.
Category: prescription | Type: HUMAN PRESCRIPTION DRUG LABEL
Date: 20260219

ACTIVE INGREDIENTS: PHENAZOPYRIDINE HYDROCHLORIDE 100 mg/1 1
INACTIVE INGREDIENTS: CARNAUBA WAX; CROSCARMELLOSE SODIUM; HYPROMELLOSES; MAGNESIUM STEARATE; CELLULOSE, MICROCRYSTALLINE; POLYETHYLENE GLYCOL 1000; POVIDONE; STARCH, CORN

PHENAZOPYRIDINE HYDROCHLORIDE TABLETS, USP
Rx Only

CAUTION: Federal law prohibits dispensing without prescription.

DESCRIPTION

Phenazopyridine Hydrochloride, USP is light or dark red to dark violet, odorless, slightly bitter, crystalline powder. It has a specific local analgesic effect in the urinary tract, promptly relieving burning and pain. It has the following structural formula:

C11H11N5•HCl M.W. 249.70

Phenazopyridine HCl tablets, USP contain the following inactive ingredients: carnauba wax, croscarmellose sodium, hypromellose, magnesium stearate, microcrystalline cellulose, polyethylene glycol, povidone, pregelatinized starch.

CLINICAL PHARMACOLOGY

Phenazopyridine HCl is excreted in the urine where it exerts a topical analgesic effect on the mucosa of the urinary tract. This action helps to relieve pain, burning, urgency and frequency. The precise mechanism of action is not known.

The pharmacokinetic properties of Phenazopyridine HCl have not been determined. Phenazopyridine HCl is rapidly excreted by the kidneys, with as much as 66% of an oral dose being excreted unchanged in the urine.

INDICATIONS AND USAGE

Phenazopyridine HCl is indicated for the symptomatic relief of pain, burning, urgency, frequency, and other discomforts arising from irritation of the lower urinary tract mucosa caused by infection, trauma, surgery, endoscopic procedures, or the passage of sounds or catheters. The use of Phenazopyridine HCl for relief of symptoms should not delay definitive diagnosis and treatment of causative conditions. Because it provides only symptomatic relief, prompt appropriate treatment of the cause of pain must be instituted and Phenazopyridine HCl should be discontinued when symptoms are controlled.

The analgesic action may reduce or eliminate the need for systemic analgesics or narcotics. It is, however, compatible with antibacterial therapy and can help to relieve pain and discomfort during the interval before antibacterial therapy controls the infection. Treatment of a urinary tract infection with Phenazopyridine HCl should not exceed 2 days because there is a lack of evidence that the combined administration of Phenazopyridine HCl and an antibacterial provides greater benefit than administration of the antibacterial alone after 2 days (see DOSAGE AND ADMINISTRATION section).

CONTRAINDICATIONS

Phenazopyridine HCl should not be used in patients who have previously exhibited hypersensitivity to it. The use of Phenazopyridine HCl is contraindicated in patients with renal insufficiency.

ADVERSE REACTIONS

Headache, rash, pruritus and occasional gastrointestinal disturbance. An anaphylactoid-like reaction has been described. Methemoglobinemia, hemolytic anemia, renal and hepatic toxicity have been reported, usually at overdosage levels (see OVERDOSAGE section).

To report SUSPECTED ADVERSE REACTIONS, contact Amneal Pharmaceuticals at 1-877-835-5472 or FDA at 1-800-FDA-1088 or www.fda.gov/medwatch.

PRECAUTIONS

General

A yellowish tinge of the skin or sclera may indicate accumulation due to impaired renal excretion and the need to discontinue therapy. The decline in renal function associated with advanced age should be kept in mind.

NOTE: Patients should be informed that Phenazopyridine HCl produces a reddish-orange discoloration of the urine and may stain fabric. Staining of contact lenses has been reported.

Laboratory Test Interaction

Due to its properties as an azo dye, Phenazopyridine HCl may interfere with urinalysis based on spectrometry or color reactions.

Carcinogenicity, Mutagenicity, Impairment of Fertility

Long-term administration of Phenazopyridine HCl has induced neoplasia in rats (large intestine) and mice (liver).

Although no association between Phenazopyridine HCl and human neoplasia has been reported, adequate epidemiological studies along these lines have not been conducted.

Pregnancy

Reproduction studies have been performed in rats at doses up to 50 mg/kg/day and have revealed no evidence of impaired fertility or harm to the fetus due to Phenazopyridine HCl. There are, however, no adequate and well controlled studies in pregnant women. Because animal reproduction studies are not always predictive of human response, this drug should be used during pregnancy only if clearly needed.

Nursing Mothers

No information is available on the appearance of Phenazopyridine HCl, or its metabolites in human milk.

DOSAGE AND ADMINISTRATION

100 mg Tablets: Average adult dosage is two tablets 3 times a day after meals.

200 mg Tablets: Average adult dosage is one tablet 3 times a day after meals.

When used concomitantly with an antibacterial agent for the treatment of a urinary tract infection, the administration of Phenazopyridine HCl should not exceed 2 days.

OVERDOSAGE

Exceeding the recommended dose in patients with good renal function or administering the usual dose to patients with impaired renal function (common in elderly patients) may lead to increased serum levels and toxic reactions. Methemoglobinemia generally follows a massive, acute overdose. Methylene blue, 1 to 2 mg/kg/body weight intravenously or ascorbic acid 100 to 200 mg given orally should cause prompt reduction of the methemoglobinemia and disappearance of the cyanosis which is an aid in diagnosis. Oxidative Heinz body hemolytic anemia may also occur, and “bite cells” (degmacytes) may be present in a chronic overdosage situation. Red blood cell G-6-PD deficiency may predispose to hemolysis. Renal and hepatic impairment and occasional failure, usually due to hypersensitivity, may also occur.

HOW SUPPLIED

Phenazopyridine HCl tablets, USP 100 mg are available as deep brown to maroon colored, round, film-coated tablets debossed PY above 1 on one side and plain on the other.

NDC 68071-2357-4 BOTTLES OF 4
NDC 68071-2357-8 BOTTLES OF 8

NDC 68071-2357-2 BOTTLES OF 12

DISPENSE contents with a child-resistant closure (as required) and in a tight container as defined in the USP.

STORE at 20° to 25°C (68° to 77°F); excursions permitted between15° to 30°C (59° to 86°F) [see USP Controlled Room Temperature].

Distributed by:
Amneal Pharmaceuticals LLC
Bridgewater, NJ 08807

Rev. 06-2020-01